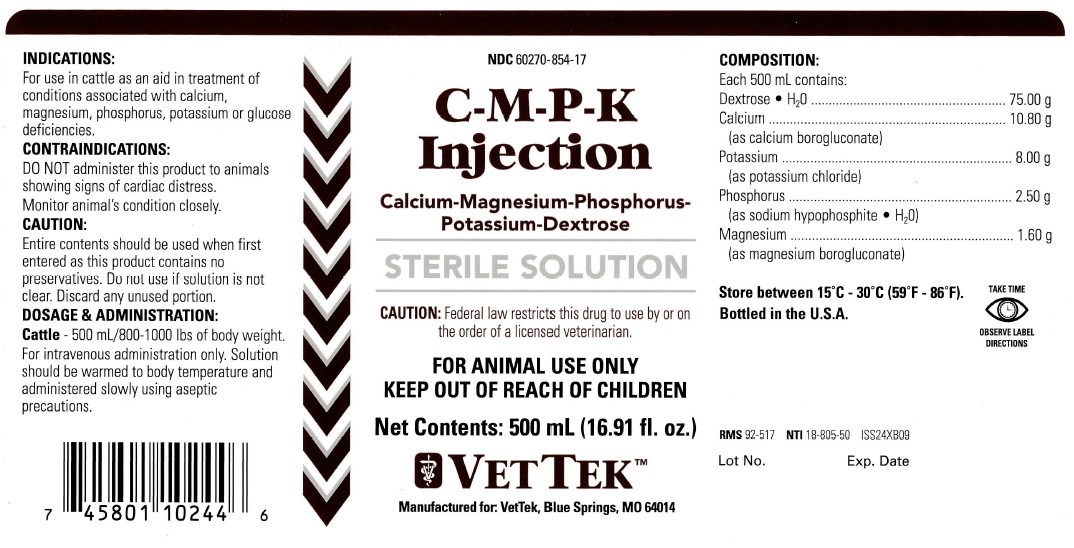 DRUG LABEL: C-M-P-K
NDC: 60270-854 | Form: INJECTION, SOLUTION
Manufacturer: VetTek
Category: animal | Type: PRESCRIPTION ANIMAL DRUG LABEL
Date: 20250708

ACTIVE INGREDIENTS: CALCIUM GLUCONATE MONOHYDRATE 10.8 g/500 mL; POTASSIUM CHLORIDE 8.0 g/500 mL; PHOSPHORUS 2.5 g/500 mL; MAGNESIUM GLUCONATE 1.6 g/500 mL; DEXTROSE MONOHYDRATE 75.0 g/500 mL

C-M-P-K Injection

KEEP OUT OF REACH OF CHILDREN

INDICATIONS:

For use in cattle as an aid in treatment of conditions associated with calcium, magnesium, phosphorus, potassium or glucose deficiencies.

CONTRAINDICATIONS:

Do not administer this product to animals showing signs of cardiac distress. Monitor animal's condition closely.

CAUTION:

Entire contents should be used when first entered as this product contains no preservatives. Do not use if solution is not clear. Discard any unused portion.

DOSAGE AND ADMINISTRATION:

Cattle - 500 mL/800-1000 lbs of body weight. For intravenous administration only. Solution should be warmed to body temperature and administered slowly using aspetic precautions.

STORAGE AND HANDLING

Store between 15°C - 30°C (59°F - 86°F).

VETERINARY INDICATIONS

For Animal Use Only

TAKE TIME OBSERVE LABEL DIRECTIONS

CAUTION:

Federal law restricts this drug to use by or on the order of a licensed veterinarian.

COMPOSITION:

Each 500 mL contains:
Dextrose • H2O.............................75.00 g

Calcium .......................................10.80 g
(as calcium borogluconate)
Potassium......................................8.00 g
(as potassium chloride)
Phosphorus ...................................2.50 g
(as sodium hypophosphite • H2O)
Magnesium ...................................1.60 g
(as magnesium borogluconate)

INFORMATION FOR OWNERS/CAREGIVERS

NDC 60270-854-17

Manufactured for: VetTek, Blue Springs, MO 64014

CALCIUM-MAGNESIUM-PHOSPHORUS-POTASSIUM-DEXTROSE

STERILE SOLUTION

NET CONTENTS: 500 mL (16.91 fl. oz.)

Bottled in the U.S.A.

RMS 92-517 NTI 18-805 ISS24XB09

Lot No. Exp. Date